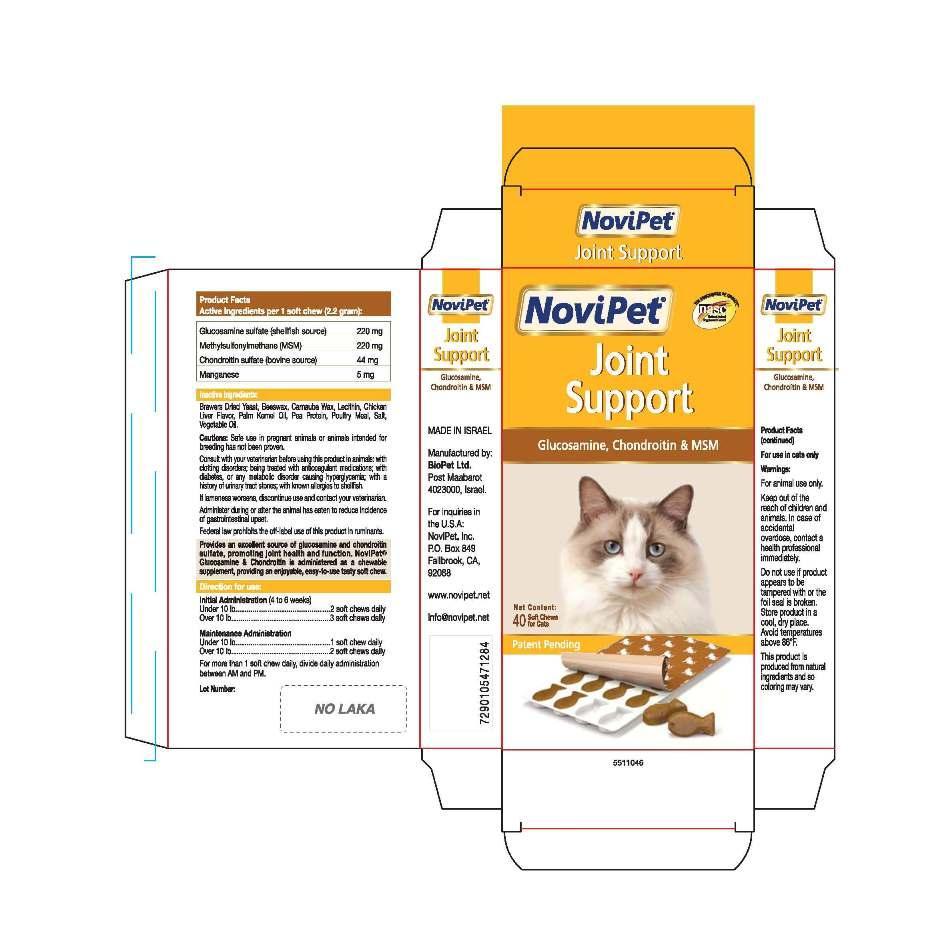 DRUG LABEL: Novipet
NDC: 45732-046 | Form: TABLET, CHEWABLE
Manufacturer: Novipet, Inc.
Category: animal | Type: OTC ANIMAL DRUG LABEL
Date: 20130521

ACTIVE INGREDIENTS: GLUCOSAMINE SULFATE 220 mg/1 1; CHONDROITIN SULFATE SODIUM (BOVINE) 44 mg/1 1; DIMETHYL SULFONE 220 1/1 1; MANGANESE 5 mg/1 1

NoviPet Joint Support for Cats

FRONT PANEL

NoviPet

Joint

Support

Glucosamine, Chondroitin and MSM

Net Content:

40 Soft Chews

for Cats

Patent Pending

Back Panel

Product Facts

Active Ingredients per 1 soft chew (2.2 gram):

Glucosamine sulfate (shellfish source) | 220 mg
Methylsulfonylmethane (MSM) | 220 mg
Chondroitin sulfate (bovine source) | 44 mg
Manganese | 5 mg

Inactive Ingredients:

Brewers Dried Yeast, Beeswax, Carnauba Wax, Lecithin, Chicken

Liver Flavor, Palm Kernel Oil, Pea Protein, Poultry Meal, Salt,

Vegetable Oil.

Cautions: Safe use in pregnant animals or animals intended for

breeding has not been proven.

Consult with your veterinarian before using this product in animals: with

clotting disorders; being treated with anticoagulant medications; with

diabetes, or any metabolic disorder causing hypoglycemia; with a

history of urinary tract stones; with known allergies to shellfish.

If lameness worsens, discontinue use and contact your veterinarian.

Federal law prohibits the off-label use of this product in ruminants.

Provides an excellent source of glucosamine and chondroitin
sulfate, promoting joint health and function. NovlPet®
Glucosamine and Chondroitin is administered as a chewable
supplement, providing an enjoyable, easy-to-use tasty soft chew.

Directions for use:

Initial Administration (4 to 6 weeks)

Under 10 lb | 2 soft chews daily
Over 10 lb | 3 soft chews daily

Maintenance Administration

Under 10 lb | 1 soft chew daily
Over 10 lb | 2 soft chews daily

For more than 1 soft chew daily, divide daily administation

between AM and PM

Lot Number:

LEFT SIDE PANEL

NoviPet

Joint Support

Glucosamine,

Chondroitin, and MSM

MADE IN ISRAEL

Manufactured by:

BioPet ltd.

Post Maabarot

4023000, Israel.

For inquiries in

the U.S.A.:

NoviPet, Inc.

P.O. Box 849

Fallbrook, CA,

92088

www.novipet.net

info@novipet.net

RIGHT SIDE PANEL

NoviPet

Joint

Support

Glucosamine

Chondroitin and MSM

Product Facts (continued)

For use in cats only

Warnings:

For animal use only.

Keep out of the

reach of children and

animals. In case of

accidental

overdose, contact a

health professional

immediately.

Do not use if product

appears to be

tampered with or the

foil seal is broken.

Store product in a

cool, dry place.

Avoid temperatures

above

86^0F.

This product is

produced from natural

ingredients and so

coloring may vary.

PACKAGE LABEL

Novipet Joint Cat